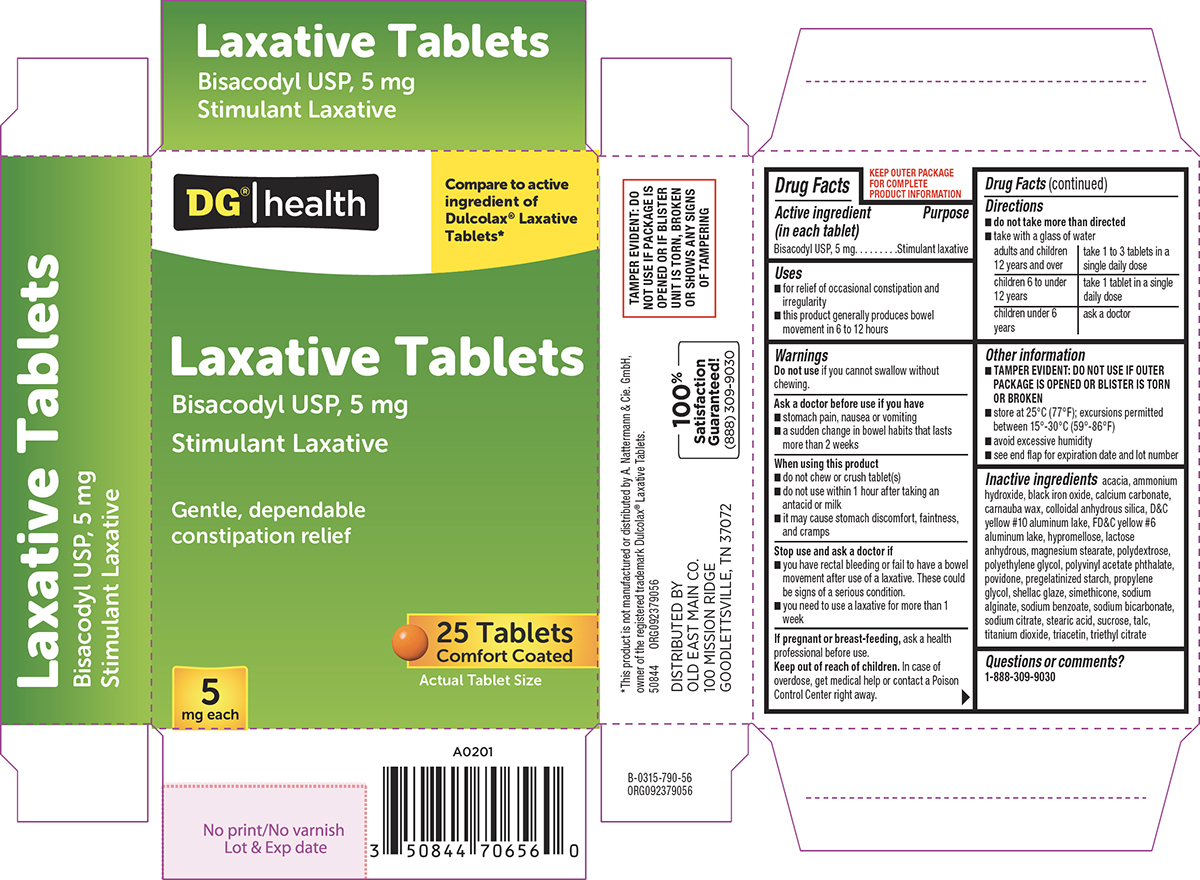 DRUG LABEL: Laxative
NDC: 55910-792 | Form: TABLET, DELAYED RELEASE
Manufacturer: DOLGENCORP, LLC
Category: otc | Type: HUMAN OTC DRUG LABEL
Date: 20260106

ACTIVE INGREDIENTS: BISACODYL 5 mg/1 1
INACTIVE INGREDIENTS: ACACIA; AMMONIA; FERROSOFERRIC OXIDE; CALCIUM CARBONATE; CARNAUBA WAX; SILICON DIOXIDE; D&C YELLOW NO. 10 ALUMINUM LAKE; FD&C YELLOW NO. 6 ALUMINUM LAKE; HYPROMELLOSE, UNSPECIFIED; ANHYDROUS LACTOSE; MAGNESIUM STEARATE; POLYDEXTROSE; POLYETHYLENE GLYCOL, UNSPECIFIED; Polyvinyl Acetate Phthalate; POVIDONE, UNSPECIFIED; STARCH, CORN; PROPYLENE GLYCOL; SHELLAC; DIMETHICONE; WATER; SODIUM ALGINATE; SODIUM BENZOATE; SODIUM BICARBONATE; SODIUM CITRATE; STEARIC ACID; SUCROSE; TALC; TITANIUM DIOXIDE; TRIACETIN; TRIETHYL CITRATE

Dollar General 44-790

Active ingredient (in each tablet)

Bisacodyl USP, 5 mg

Purpose

Stimulant laxative

Uses

- for relief of occasional constipation and irregularity
- this product generally produces bowel movement in 6 to 12 hours

Warnings

Do not use

if you cannot swallow without chewing.

Ask a doctor before use if you have

- stomach pain, nausea or vomiting
- a sudden change in bowel habits that lasts more than 2 weeks

When using this product

- do not chew or crush tablet(s)
- do not use within 1 hour after taking an antacid or milk
- it may cause stomach discomfort, faintness, and cramps

Stop use and ask a doctor if

- you have rectal bleeding or fail to have a bowel movement after use of a laxative. These could be signs of a serious condition.
- you need to use a laxative for more than 1 week

If pregnant or breast-feeding,

ask a health professional before use.

Keep out of reach of children.

In case of overdose, get medical help or contact a Poison Control Center right away.

Directions

- do not take more than directed
- take with a glass of water

adults and children 12 years and over | take 1 to 3 tablets in a single daily dose
children 6 to under 12 years | take 1 tablet in a single daily dose
children under 6 years | ask a doctor

Other information

- TAMPER EVIDENT: DO NOT USE IF OUTER PACKAGE IS OPENED OR BLISTER IS TORN OR BROKEN
- store at 25°C (77°F); excursions permitted between 15°-30°C (59°-86°F)
- avoid excessive humidity
- see end flap for expiration date and lot number

Inactive ingredients

acacia, ammonium hydroxide, black iron oxide, calcium carbonate, carnauba wax, colloidal anhydrous silica, D&C yellow #10 aluminum lake, FD&C yellow #6 aluminum lake, hypromellose, lactose anhydrous, magnesium stearate, polydextrose, polyethylene glycol, polyvinyl acetate phthalate, povidone, pregelatinized starch, propylene glycol, shellac glaze, simethicone, sodium alginate, sodium benzoate, sodium bicarbonate, sodium citrate, stearic acid, sucrose, talc, titanium dioxide, triacetin, triethyl citrate

Questions or comments?

1-888-309-9030

Principal display panel

DG® | health

Compare to active
ingredient of
Dulcolax® Laxative
Tablets*

Laxative Tablets
Bisacodyl USP, 5 mg
Stimulant Laxative

Gentle, dependable
constipation relief

5
mg each

25 Tablets
Comfort Coated

Actual Tablet Size

TAMPER EVIDENT: DO
NOT USE IF PACKAGE IS
OPENED OR IF BLISTER
UNIT IS TORN, BROKEN
OR SHOWS ANY SIGNS
OF TAMPERING

*This product is not manufactured or distributed by A. Nattermann & Cie. GmbH,
owner of the registered trademark Dulcolax® Laxative Tablets.
50844 ORG092379056

DISTRIBUTED BY
OLD EAST MAIN CO.
100 MISSION RIDGE
GOODLETTSVILLE, TN 37072

100% Satisfaction
Guaranteed!
(888)309-9030

Dollar General 44-790